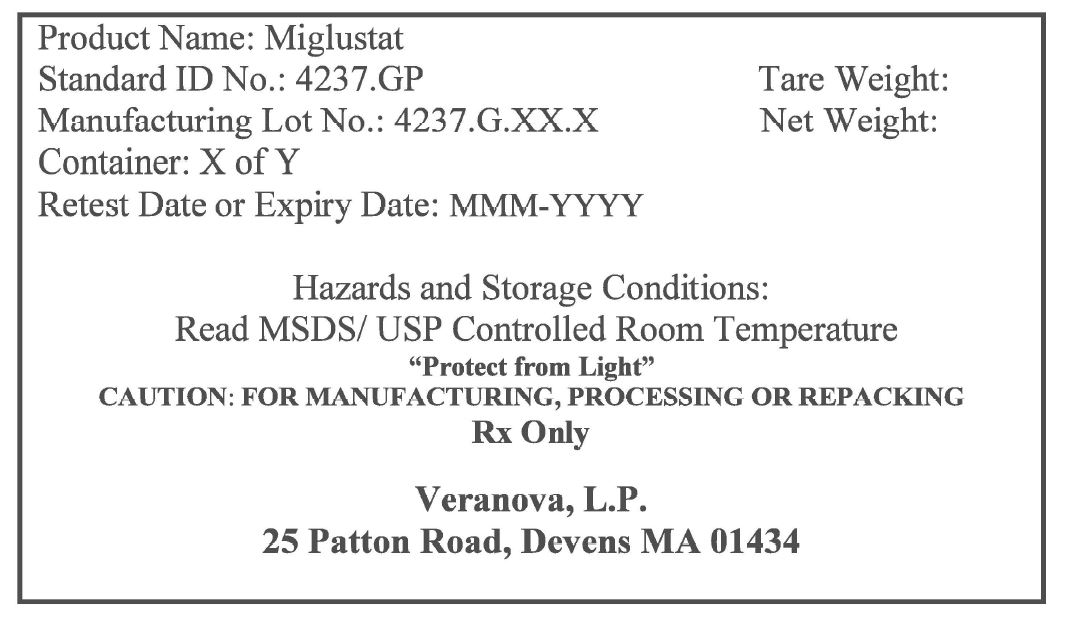 DRUG LABEL: MIGLUSTAT
NDC: 50137-4237 | Form: POWDER
Manufacturer: Veranova, L.P.
Category: other | Type: BULK INGREDIENT
Date: 20221109

ACTIVE INGREDIENTS: MIGLUSTAT 1 kg/1 kg

Miglustat (4237.G)